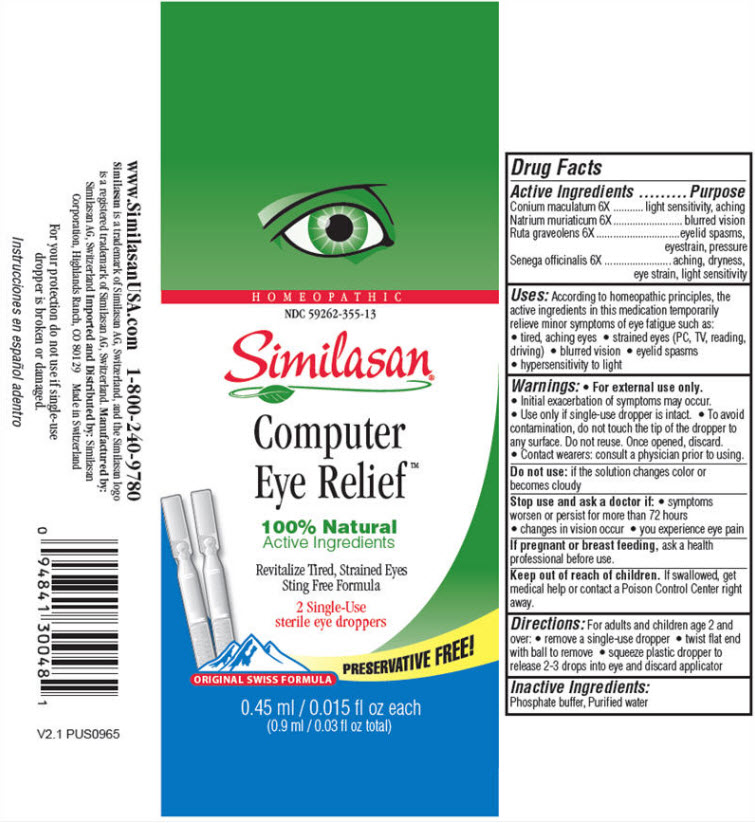 DRUG LABEL: Computer Eye Relief
NDC: 59262-355 | Form: SOLUTION/ DROPS
Manufacturer: Similasan Corporation
Category: homeopathic | Type: HUMAN OTC DRUG LABEL
Date: 20190320

ACTIVE INGREDIENTS: CONIUM MACULATUM FLOWERING TOP 6 [hp_X]/0.45 mL; SODIUM CHLORIDE 6 [hp_X]/0.45 mL; RUTA GRAVEOLENS FLOWERING TOP 6 [hp_X]/0.45 mL; POLYGALA SENEGA ROOT 6 [hp_X]/0.45 mL
INACTIVE INGREDIENTS: WATER; SODIUM PHOSPHATE, MONOBASIC, DIHYDRATE; SODIUM PHOSPHATE, DIBASIC, ANHYDROUS

Similasan Dry Eye Relief Trial Size

Active Ingredient

Conium maculatum 6X

Purpose

light sensitivity, aching

Active Ingredient

Natrium muriaticum 6X

Purpose

blurred vision

Active Ingredient

Ruta graveolens 6X

Purpose

eyelid spasms, eye strain, pressure

Active Ingredient

Senega officinalis 6X

Purpose

aching, dryness, eye strain, light sensitivity

Uses

According to homeopathic principles, the active ingredients in this medication temporarily relieve minor symptoms of eye fatigue such as:

- tired, aching eyes
- strained eyes (PC, TV, reading, driving)
- blurred vision
- eyelid spasms
- hypersensitivity to light

Warnings

- For external use only.
- Initial exacerbation of symptoms may occur.
- Use only if single-use dropper is intact.
- To avoid contamination, do not touch the tip of the dropper to any surface. Do not reuse. Once opened, discard.
- Contact wearers: consult a physician prior to using.

Do not use:

if the solution changes color or becomes cloudy

Stop use and ask a doctor if:

- symptoms worsen or persist for more than 72 hours.
- changes in vision occur.
- you experience eye pain.

If pregnant or breast feeding,

ask a health professional before use.

Keep out of reach of children.

If swallowed, get medical help or contact a Poison Control Center right away.

Directions

For adults and children age 2 and over:

- remove a single-use dropper
- twist flat end with ball to remove
- squeeze plastic dropper to release 2-3 drops into eye and discard applicator

Inactive Ingredients

Phosphate buffer, Purified water

Principal Display Panel

HOMEOPATHIC
NDC 59262-355-13
Similasan
Computer Eye ReliefTM
100% Natural Active Ingredients
2 Single-Use sterile eye droppers
0.45 ml/ 0.015 fl oz each
(0.9 ml/ 0.03 fl oz total)